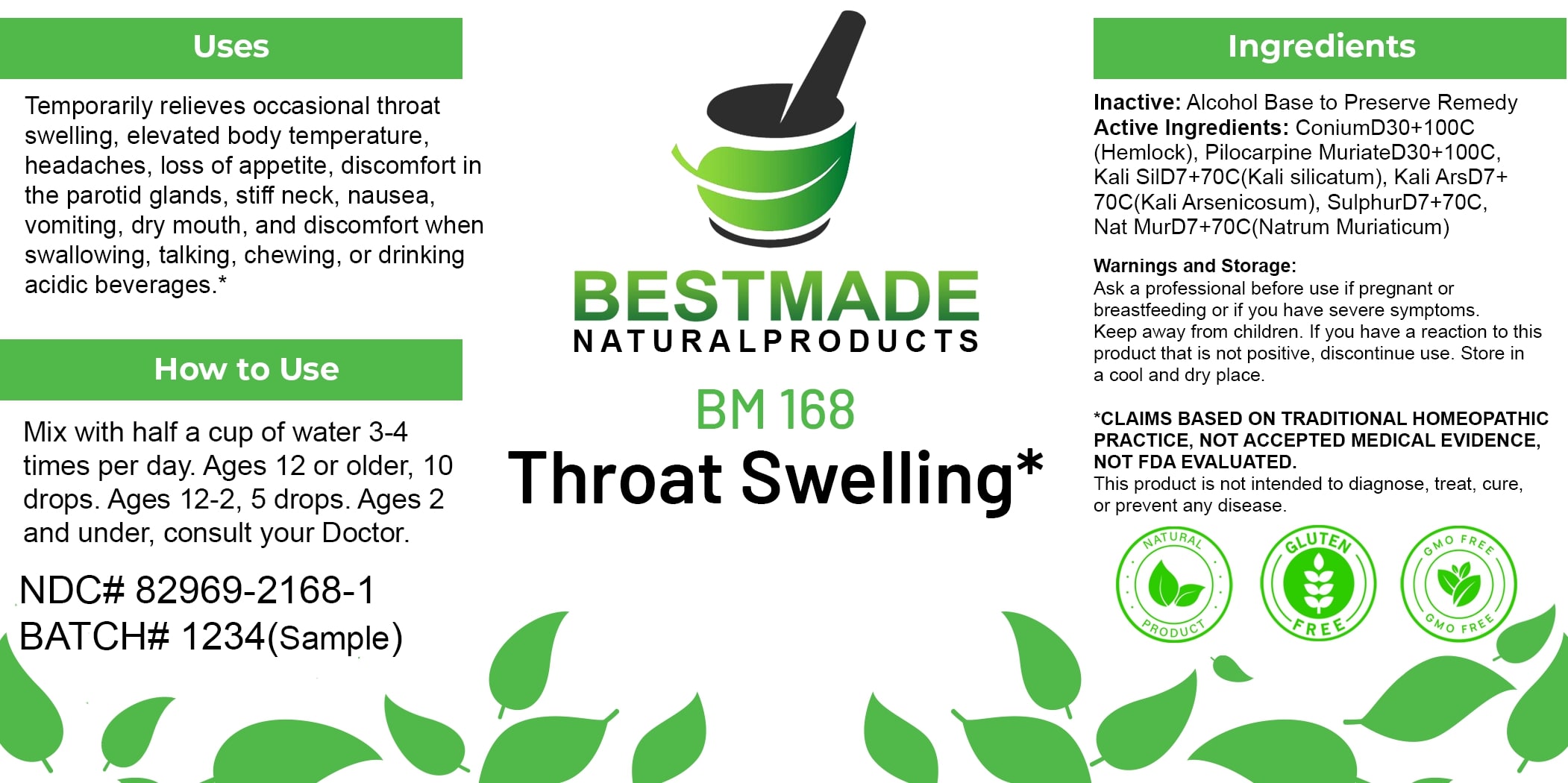 DRUG LABEL: Bestmade Natural Products BM168
NDC: 82969-2168 | Form: LIQUID
Manufacturer: Bestmade Natural Products
Category: homeopathic | Type: HUMAN OTC DRUG LABEL
Date: 20250219

ACTIVE INGREDIENTS: POTASSIUM SILICATE 30 [hp_C]/30 [hp_C]; POTASSIUM ARSENITE ANHYDROUS 30 [hp_C]/30 [hp_C]; SULFUR 30 [hp_C]/30 [hp_C]; SODIUM CHLORIDE 30 [hp_C]/30 [hp_C]; PILOCARPINE HYDROCHLORIDE 30 [hp_C]/30 [hp_C]; CONIUM MACULATUM FLOWERING TOP 30 [hp_C]/30 [hp_C]
INACTIVE INGREDIENTS: ALCOHOL 30 [hp_C]/30 [hp_C]

BM168

DOSAGE AND ADMINISTRATION

How to Use

Mix with half a cup of water 3-4 times per day. Ages 12 or older, 10 drops. Ages 12-2, 5 drops. Ages 2 and under, consult your Doctor.

ACTIVE INGREDIENT

Active Ingredients: ConiumD10+100C (Hemlock), Pilocarpine MuriateD30+100C, Kali SilD7+70C(Kali Silicatum), Kali ArsD7+ 70C(Kali Arsenicosum), SulphurD7+70C, Nat MurD7+70C(Natrum Muriaticum)

INACTIVE INGREDIENT

Ingredients

Inactive: Alcohol Base to Preserve Remedy

Uses

Temporarily relieves occasional throat swelling, elevated body temperature, headaches, loss of appetite, discomfort in the parotid glands, stiff neck, nausea, vomiting, dry mouth, and discomfort when swallowing, talking, chewing, or drinking acidic beverages.*

*CLAIMS BASED ON TRADITIONAL HOMEOPATHIC PRACTICE, NOT ACCEPTED MEDICAL EVIDENCE. NOT FDA EVALUATED.

This product is not intended to diagnose, treat, cure, or prevent any disease.

Uses

Temporarily relieves occasional throat swelling, elevated body temperature, headaches, loss of appetite, discomfort in the parotid glands, stiff neck, nausea, vomiting, dry mouth, and discomfort when swallowing, talking, chewing, or drinking acidic beverages.*

*CLAIMS BASED ON TRADITIONAL HOMEOPATHIC PRACTICE, NOT ACCEPTED MEDICAL EVIDENCE. NOT FDA EVALUATED.

This product is not intended to diagnose, treat, cure, or prevent any disease.

KEEP OUT OF REACH OF CHILDREN

Warnings and Storage:

Ask a professional before use if pregnant or breastfeeding or if you have severe symptoms. Keep away from children. If you have a reaction to this product that is not positive, discontinue use. Store in a cool and dry place.

Warnings and Storage:

Ask a professional before use if pregnant or breastfeeding or if you have severe symptoms. Keep away from children. If you have a reaction to this product that is not positive, discontinue use. Store in a cool and dry place.

*CLAIMS BASED ON TRADITIONAL HOMEOPATHIC PRACTICE, NOT ACCEPTED MEDICAL EVIDENCE. NOT FDA EVALUATED.

This product is not intended to diagnose, treat, cure, or prevent any disease.

Entire package label